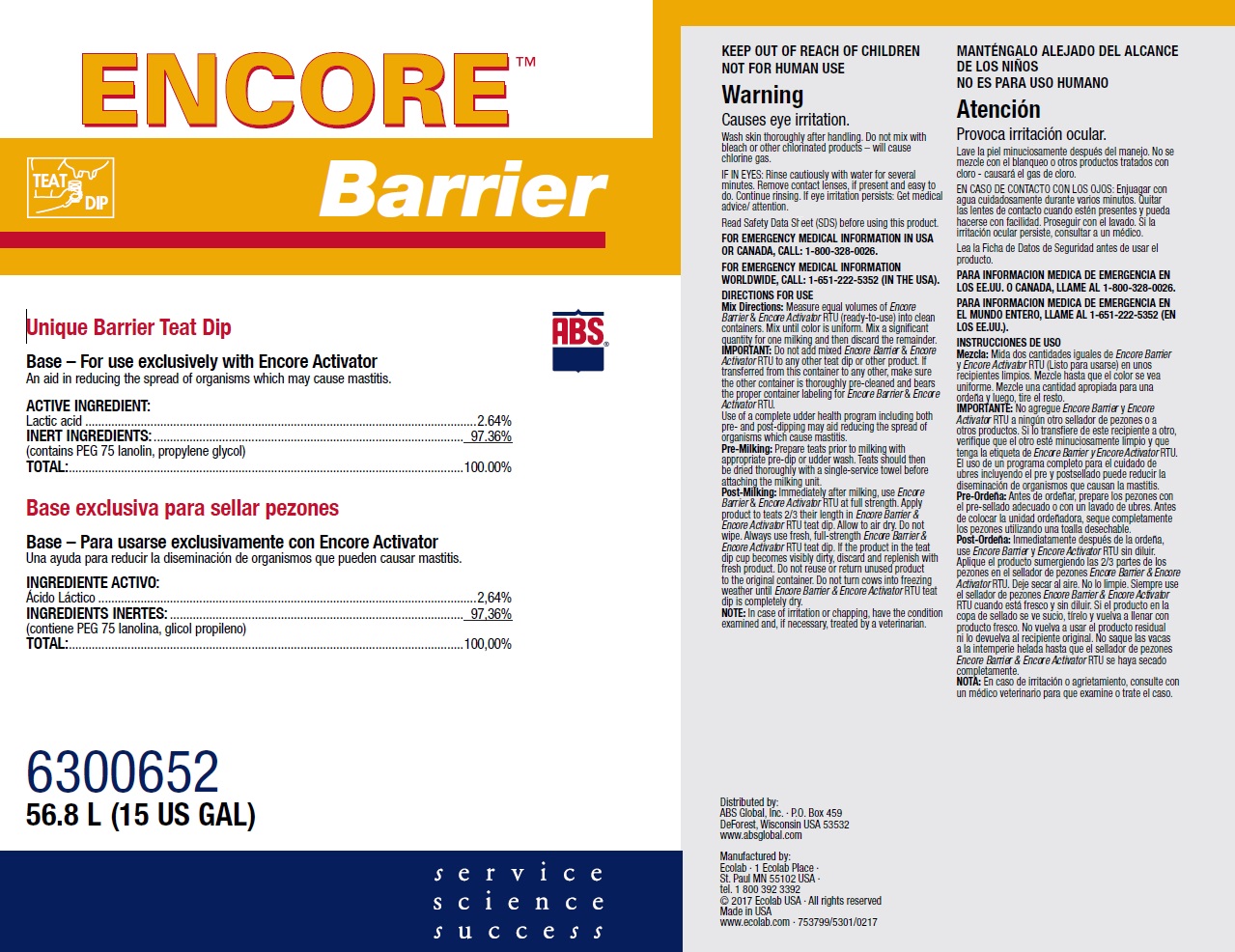 DRUG LABEL: Encore
NDC: 59282-106 | Form: SOLUTION
Manufacturer: ABS Global Inc.
Category: animal | Type: OTC ANIMAL DRUG LABEL
Date: 20211029

ACTIVE INGREDIENTS: LACTIC ACID 26.4 mg/1 mL
INACTIVE INGREDIENTS: PROPYLENE GLYCOL; PEG-75 LANOLIN

KEEP OUT OF REACH OF CHILDREN

NOT FOR HUMAN USE

Warning

Causes eye irritation.

Wash skin thoroughly after handling. Do not mix with bleach or other chlorinated products – will cause chlorine gas.

OTHER SAFETY INFORMATION

IF IN EYES: Rinse cautiously with water for several minutes. Remove contact lenses, if present and easy to do. Continue rinsing. If eye irritation persists: Get medical advice/ attention.

Read Safety Data Sheet (SDS) before using this product.

FOR EMERGENCY MEDICAL INFORMATION IN USA OR CANADA, CALL: 1-800-328-0026.

FOR EMERGENCY MEDICAL INFORMATION WORLDWIDE, CALL: 1-651-222-5352 (IN THE USA).

VETERINARY INDICATIONS

DIRECTIONS FOR USE

Mix Directions: Measure equal volumes of Encore Barrier & Encore Activator RTU (ready-to-use) into clean containers. Mix until color is uniform. Mix a significant quantity for one milking and then discard the remainder.

IMPORTANT: Do not add mixed Encore Barrier & Encore Activator RTU to any other teat dip or other product. If transferred from this container to any other, make sure the other container is thoroughly pre-cleaned and bears the proper container labeling for Encore Barrier & Encore Activator RTU.
Use of a complete udder health program including both pre- and post-dipping may aid reducing the spread of organisms which cause mastitis.

Pre-Milking: Prepare teats prior to milking with appropriate pre-dip or udder wash. Teats should then be dried thoroughly with a single-service towel before attaching the milking unit.

Post-Milking: Immediately after milking, use Encore Barrier & Encore Activator RTU at full strength. Apply product to teats 2/3 their length in Encore Barrier & Encore Activator RTU teat dip. Allow to air dry. Do not wipe. Always use fresh, full-strength Encore Barrier & Encore Activator RTU teat dip. If the product in the teat dip cup becomes visibly dirty, discard and replenish with fresh product. Do not reuse or return unused product to the original container. Do not turn cows into freezing weather until Encore Barrier & Encore Activator RTU teat dip is completely dry.

NOTE: In case of irritation or chapping, have the condition examined and, if necessary, treated by a veterinarian.

PACKAGE LABEL

ENCORE™

Barrier

ABS

Unique Barrier Teat Dip

Base – For use exclusively with Encore Activator

An aid in reducing the spread of organisms which may cause mastitis.

ACTIVE INGREDIENTS:

Lactic Acid .....................................2.64%

INERT INGREDIENTS ....................97.36%

(contains PEG 75 lanolin, propylene glycol)

Total: ...........................................100.00%

6300652

Net Contents:

56.8L (15 US GAL)